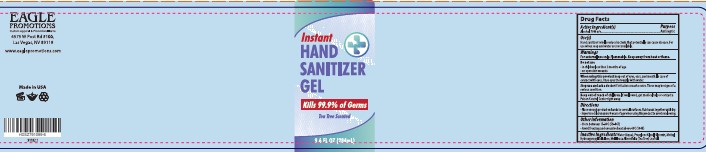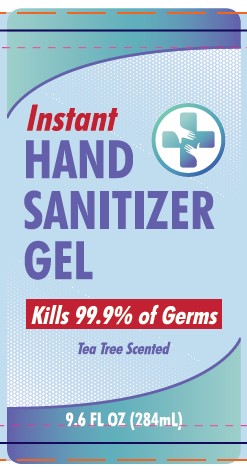 DRUG LABEL: Eagle Promotions
NDC: 73333-284 | Form: GEL
Manufacturer: Nutrix International, LLC.
Category: otc | Type: HUMAN OTC DRUG LABEL
Date: 20200521

ACTIVE INGREDIENTS: ALCOHOL 0.74 g/284 g
INACTIVE INGREDIENTS: WATER 0.233 g/284 g; TEA TREE OIL 0.002 g/284 g; GLYCERIN 0.008 g/284 g; PROPYLENE GLYCOL 0.01 g/284 g; HYPROMELLOSES 0.007 g/284 g

Active Ingredient[s]

Alcohol 70% v/v

Use[s]

Hand Sanitizer to help reduce bacteria that potentially can cause disease. For use when soap and water are not available.

Warnings

For external use only. Flammable. Keep away from heat or flame.

Do not use

- On children less than 2 months of age.
- On open skin wounds.

When using

Keep out of eyes, ears, and mouth. In case of contact with eyes, rinse eyes thoroughly with water.

Stop use

If irritation or rash occurs. These may be signs of a serious condition.

Keep out of reach of children

If swallowed, get medical help or contact a Poison Control Center right away.

Directions

- Place enough product on hands to cover all surfaces.
- Rub hands together until dry.
- Supervise children under 6 years of age.
- When using this product avoid swallowing.

Other Information

- Store between 15-30°C (59-86°F)
- Avoid freezing and excessive heat above 40°C (104°F)

Inactive Ingredients

Water (Aqua), Propylene Glycol, Glycerin, Methyl Hydroxypropyl Cellulose, Melaleuca Alternifolia (Tea Tree) Leaf Oil.

Purpose

Antiseptic

Package

Full Package label